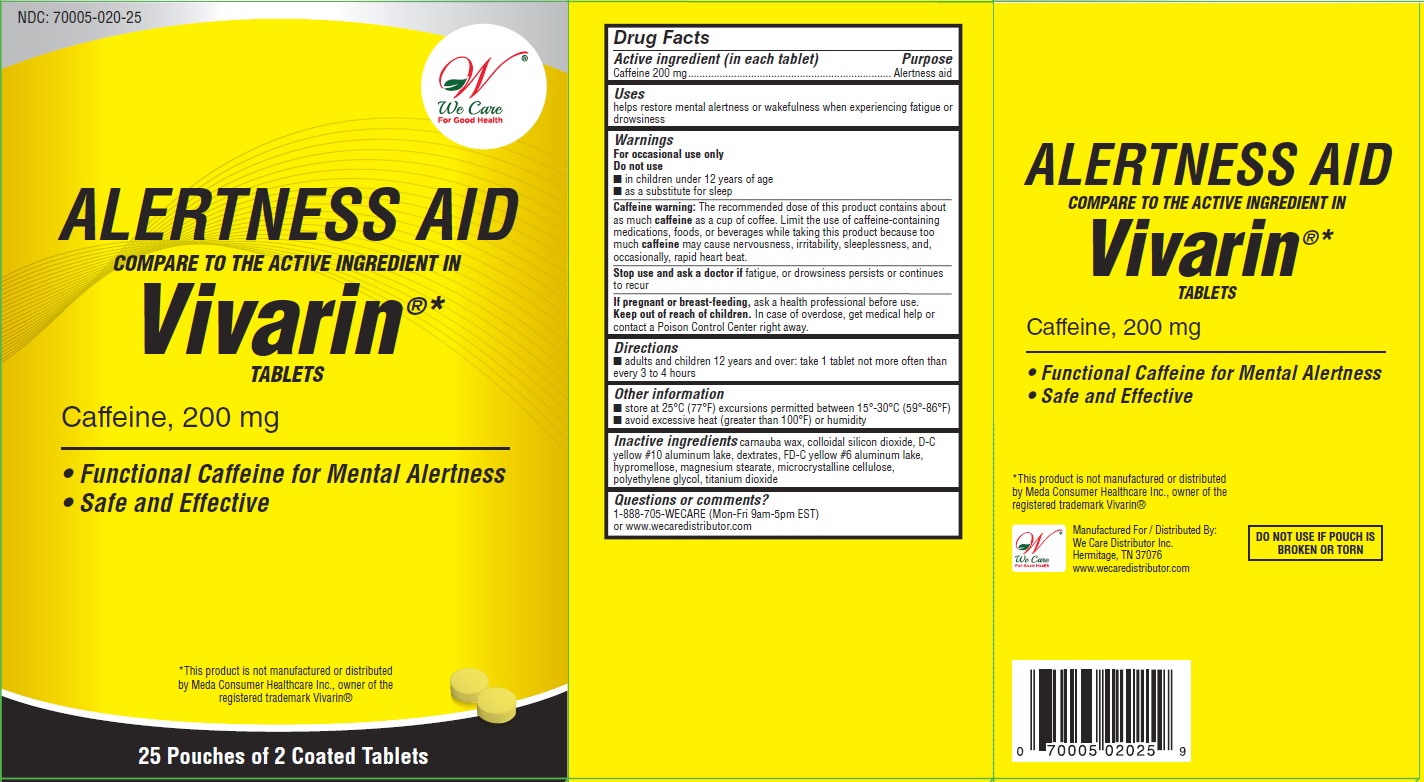 DRUG LABEL: ALERTNESS AID 
NDC: 70005-020 | Form: TABLET, COATED
Manufacturer: We Care Distributor Inc.
Category: otc | Type: HUMAN OTC DRUG LABEL
Date: 20160308

ACTIVE INGREDIENTS: CAFFEINE 200 mg/1 1
INACTIVE INGREDIENTS: CARNAUBA WAX; SILICON DIOXIDE; D&C YELLOW NO. 10; DEXTRATES; FD&C YELLOW NO. 6; HYPROMELLOSES; CELLULOSE, MICROCRYSTALLINE; MAGNESIUM STEARATE; MALTODEXTRIN; POLYETHYLENE GLYCOL 1000; TITANIUM DIOXIDE

ALERTNESS AID - Caffeine Tablets, 200 mg

Drug Facts

ACTIVE INGREDIENT

Active ingredient (in each tablet) Purpose

Caffeine 200 mg........................................Alertness aid

Uses

helps restore mental alertness or wakefulness when experiencing fatigue or drowsiness

Warnings

For occasional use only

Do not use

■ in children under 12 years of age

■ as a substitute for sleep

Caffeine warning

the recommended dose of this product contains about as much caffeine as a cup of coffee. Limit the use of caffeine-containing medications, foods, or beverages while taking this product because too much caffeine may cause nervousness, irritability, sleeplessness, and, occasionally, rapid heart beat.

Stop use and ask a doctor if

fatigue, or drowsiness persists or continues to recur

PREGNANCY OR BREAST FEEDING

If pregnant or breast-feeding, ask a health professional before use.

Keep out of reach of children.

In case of overdose, get medical help or contact a Poison Control Center right away.

Directions

■ adults and children 12 years of age or over: take 1 tablet not more often than every 3 to 4 hours

Other information

■ store at 25°C (77°F) excursions permitted between 15°-30°C (59°-86°F)

■ avoid excessive heat (greater than 100°F) or humidity

Inactive ingredients

carnauba wax, colloidal silicon dioxide, D&C yellow no10 aluminum lake, dextrates, FD&C yellow no 6 aluminum lake, hypromellose, magnesium stearate, microcrystalline cellulose, polyethylene glycol, titanium dioxide

Questions or comments?

1-888-705-WECARE (Mon-Fri 9am-5pm EST) or www.wecaredistributor.com

PRINCIPAL DISPLAY PANEL

Compare to the Active Ingredients in Vivarin®

ALERTNESS AID

Caffeine Tablets, 200 mg

TO OPEN
PUSH IN TAB AND PULL OUT

25 Pouches of 2 Tablets Each